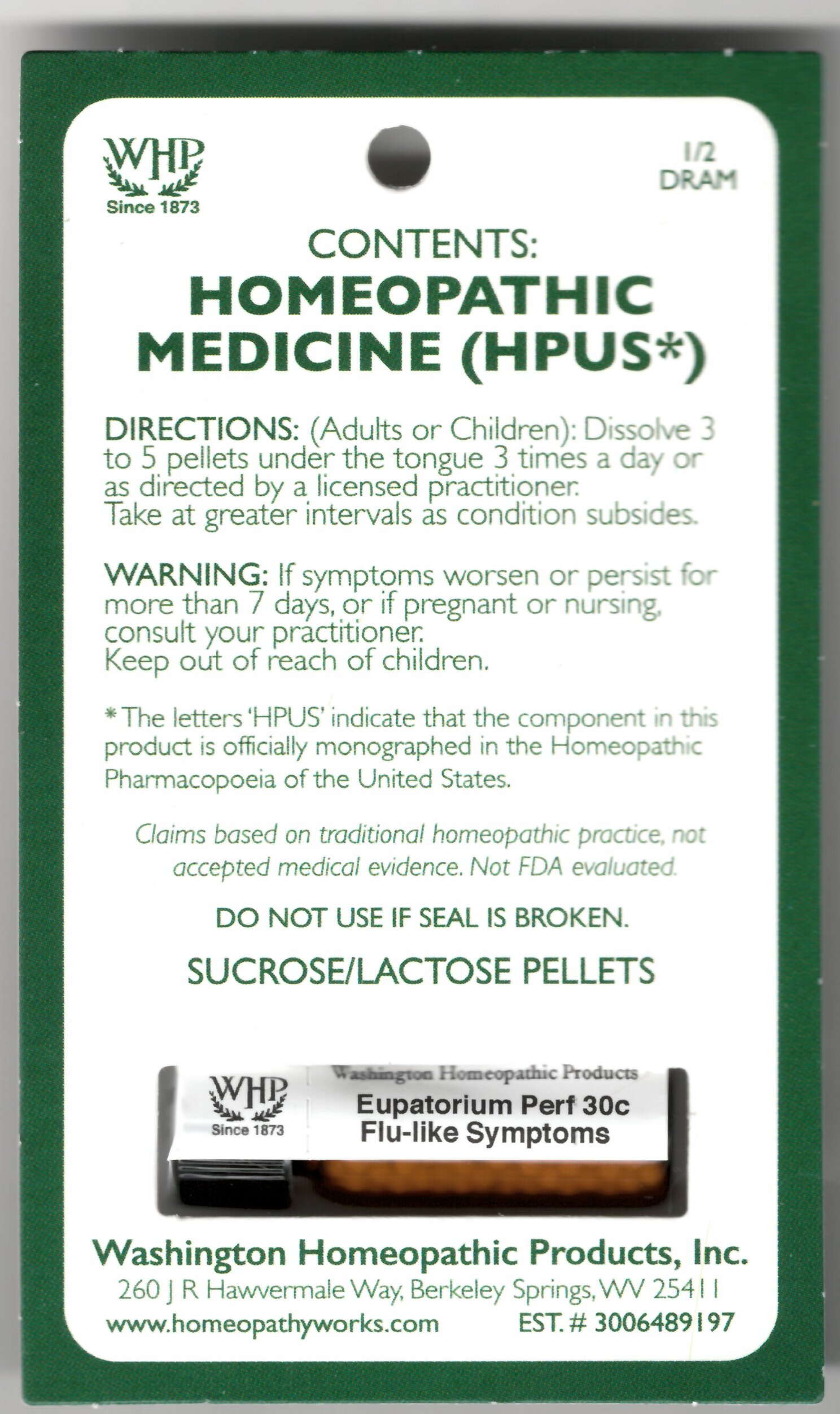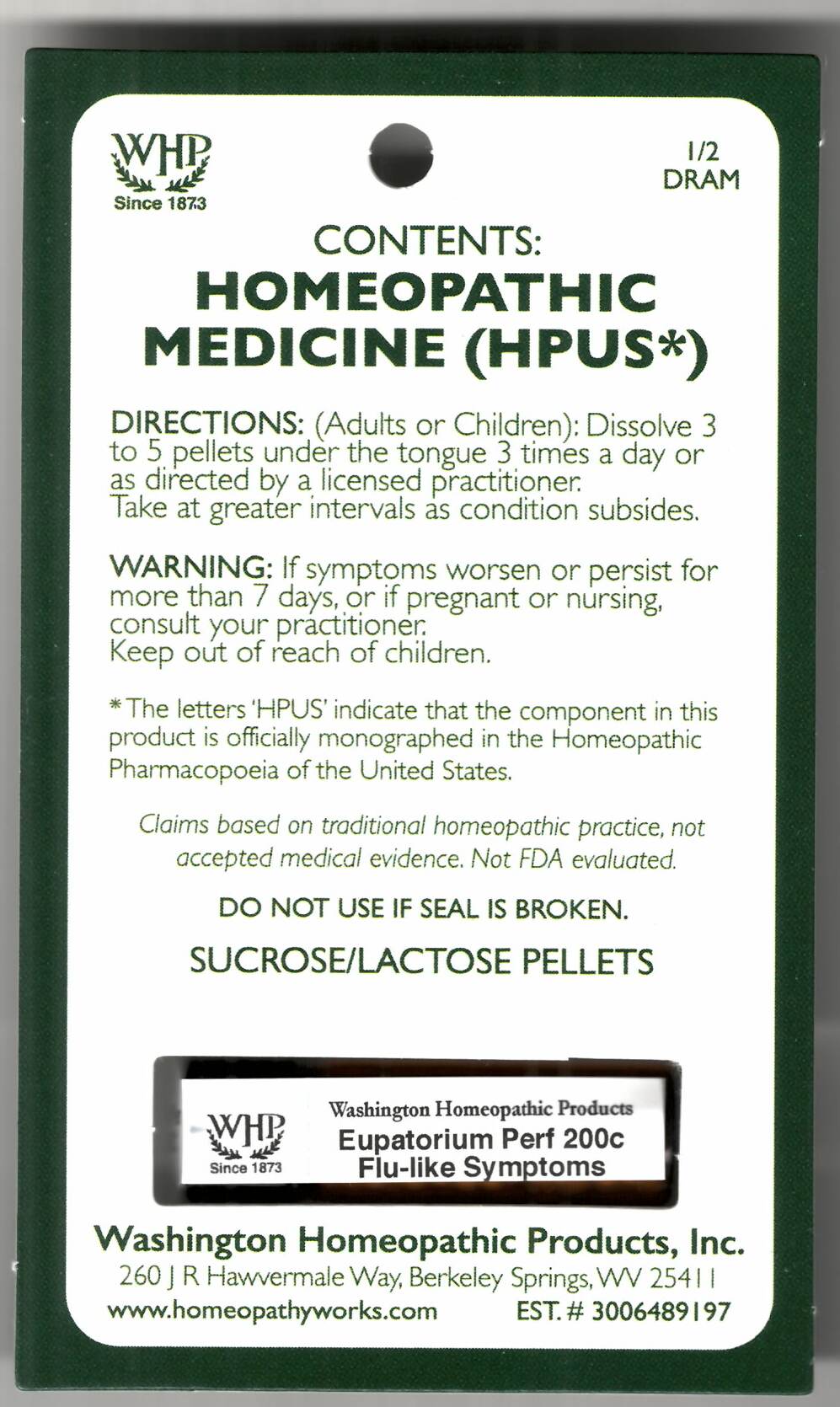 DRUG LABEL: Eupatorium Perf Kit Refill
NDC: 71919-766 | Form: PELLET
Manufacturer: Washington Homeopathic Products
Category: homeopathic | Type: HUMAN OTC DRUG LABEL
Date: 20250128

ACTIVE INGREDIENTS: EUPATORIUM PERFOLIATUM FLOWERING TOP 200 [hp_C]/1 1
INACTIVE INGREDIENTS: SUCROSE; LACTOSE

Eupatorium perfoliatum Kit Refill 200c

ACTIVE INGREDIENTS

EUPATORIUM PERF 30C

USES

To relieve the symptoms of flu-like symptoms.

KEEP OUT OF REACH OF CHILDREN

Keep this and all medicines out of reach of children.

INDICATIONS

EUPATORIUM PERF Flu-like symptoms

STOP USE AND ASK DOCTOR

If symptoms persist/worsen or if pregnant/nursing, stop use and consult your practitioner.

DIRECTIONS

Adults: Dissolve 3 to 5 under the tongue three times a day or as directed by Lic. Practitioner. Take at greater intervals as condition subsides.

Children: Dissolve 3 to 5 under the tongue three times a day or as directed by Lic. Practitioner. Take at greater intervals as condition subsides.

INACTIVE INGREDIENTS

Sucrose/Lactose